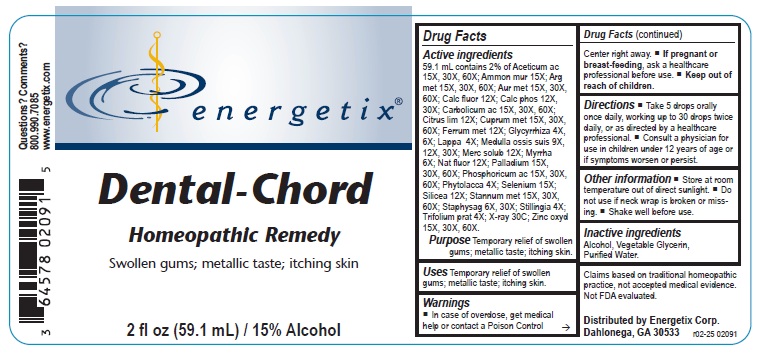 DRUG LABEL: DENTAL-CHORD
NDC: 64578-0178 | Form: LIQUID
Manufacturer: Energetix Corporation
Category: homeopathic | Type: HUMAN OTC DRUG LABEL
Date: 20250715

ACTIVE INGREDIENTS: ACETIC ACID 15 [hp_X]/59.1 mL; AMMONIUM CHLORIDE 15 [hp_X]/59.1 mL; SILVER 15 [hp_X]/59.1 mL; GOLD 15 [hp_X]/59.1 mL; CALCIUM FLUORIDE 12 [hp_X]/59.1 mL; TRIBASIC CALCIUM PHOSPHATE 12 [hp_X]/59.1 mL; PHENOL 15 [hp_X]/59.1 mL; LEMON JUICE 12 [hp_X]/59.1 mL; COPPER 15 [hp_X]/59.1 mL; IRON 12 [hp_X]/59.1 mL; GLYCYRRHIZA GLABRA 4 [hp_X]/59.1 mL; ARCTIUM LAPPA ROOT 4 [hp_X]/59.1 mL; SUS SCROFA BONE MARROW 9 [hp_X]/59.1 mL; MERCURIUS SOLUBILIS 12 [hp_X]/59.1 mL; MYRRH 6 [hp_X]/59.1 mL; SODIUM FLUORIDE 12 [hp_X]/59.1 mL; PALLADIUM 15 [hp_X]/59.1 mL; PHOSPHORIC ACID 15 [hp_X]/59.1 mL; PHYTOLACCA AMERICANA ROOT 4 [hp_X]/59.1 mL; SELENIUM 15 [hp_X]/59.1 mL; SILICON DIOXIDE 12 [hp_X]/59.1 mL; TIN 15 [hp_X]/59.1 mL; DELPHINIUM STAPHISAGRIA SEED 6 [hp_X]/59.1 mL; STILLINGIA SYLVATICA ROOT 4 [hp_X]/59.1 mL; TRIFOLIUM PRATENSE FLOWER 4 [hp_X]/59.1 mL; LACTOSE, X-RAY EXPOSED (1000 RAD) 30 [hp_C]/59.1 mL; ZINC OXIDE 15 [hp_X]/59.1 mL
INACTIVE INGREDIENTS: WATER; GLYCERIN; ALCOHOL

Dental-Chord

ACTIVE INGREDIENT

Active ingredients59.1 mL contains 2% of: Aceticum ac 15X, 30X, 60X; Ammon mur 15X; Arg met 15X, 30X, 60X; Aur met 15X, 30X, 60X; Calc fluor 12X; Calc phos 12X, 30X; Carbolicum ac 15X, 30X, 60X; Citrus lim 12X; Cuprum met 15X, 30X, 60X; Ferrum met 12X; Glycyrrhiza 4X, 6X; Lappa 4X; Medulla ossis suis 9X, 12X, 30X; Merc solub 12X; Myrrha 6X; Nat fluor 12X; Palladium 15X, 30X, 60X; Phosphoricum ac 15X, 30X, 60X; Phytolacca 4X; Selenium 15X; Silicea 12X; Stannum met 15X, 30X, 60X; Staphysag 6X, 30X; Stillingia 4X; Trifolium prat 4X; X-ray 30C; Zinc oxyd 15X, 30X, 60X.

Claims based on traditional homeopathic practice, not accepted medical evidence. Not FDA evaluated.

Uses

Temporary relief of swollen gums; metallic taste; itching skin.

Warnings

- In case of overdose, get medical help or contact a Poison Control Center right away.
- If pregnant or breast feeding, ask a healthcare professional before use.

• Keep out of reach of children.

Directions

- Take 5 drops orally once daily, working up to 30 drops twice daily, or as directed by a healthcare professional.
- Consult a physician for use in children under 12 years of age or if symptoms worsen or persist.

Other information

- Store at room temperature out of direct sunlight.
- Do not use if neck wrap is broken or missing.
- Shake well before use.

Inactive ingredients

Alcohol, Vegetable Glycerin, Purified Water.

QUESTIONS

Distributed by Energetix Corp.

Dahlonega, GA 30533

Questions? Comments?

800.990.7085

www.energetix.com

PACKAGE LABEL

energetix®

Dental-Chord

Homeopathic Remedy

Swollen gums; metallic taste; itching skin

2 fl oz (59.1 mL) / 15% Alcohol

PURPOSE

Purpose Temporary relief of swollen gums; metallic taste; itching skin.